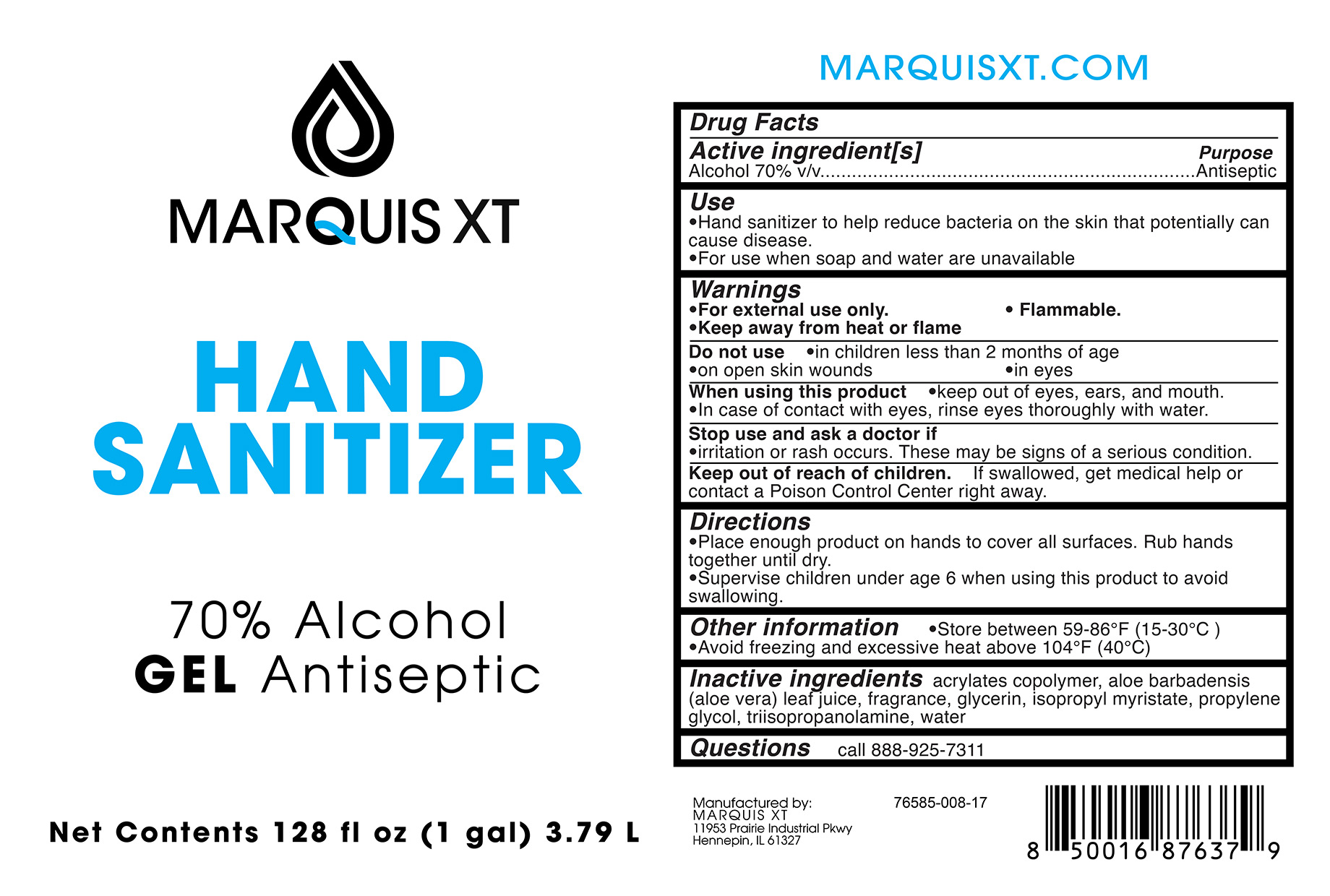 DRUG LABEL: Marquis Gel Formula
NDC: 76585-008 | Form: GEL
Manufacturer: Marquis Extraction Technology
Category: otc | Type: HUMAN OTC DRUG LABEL
Date: 20200701

ACTIVE INGREDIENTS: ALCOHOL 70 mL/100 mL
INACTIVE INGREDIENTS: ISOPROPYL MYRISTATE 0.001 mL/100 mL; CUMINYL ACETALDEHYDE 0.3 mL/100 mL; GLYCERIN 0.25 mL/100 mL; METHACRYLIC ACID - ETHYL ACRYLATE COPOLYMER (4500 MPA.S) 5 mL/100 mL; LINALOOL, (+)- 0.3 mL/100 mL; TRIISOPROPYLAMINE 0.75 mL/100 mL; ALOE VERA LEAF 0.005 mL/100 mL; PROPYLENE GLYCOL 0.25 mL/100 mL; DENATONIUM BENZOATE ANHYDROUS 0.00035 mL/100 mL

Active Ingredients

Alcohol 70% v/v Purpose Antisepic

Purpose

Antiseptic

Use

Hand sanitizer to help reduce bacteria on the skin that potentially can cause disease

For use when soap and water are unavailable

Warnings

For external use only

Flammable

Keep away from heat or flame

D not use

in children less than 2 months of age

on open skin wounds

in eyes

When using this product

Keep out of eyes, ears, and mouth

In case of contact with eyes, rinse eyes thoroughly with water

Stop use and ask a doctor if

irritation or rash occurs, these may be signs of a serious condition

Keep out of reach of children

If swallowed, get medical help or contact a Poison Control Center right away

Directions

Place enough product on hands to cover all surfaces, Rub hands together until dry.

Supervise children under the age of 6 when using this product to avoid swallowing.

Other Information

Store between 59-86F (15-30C)

Avoid freezing and excessive heat above 104F (40C)

Inactive Ingredients

acrylates copolymer, aloe barbadensis (aloe vera) leaf juice, fragrance, glycerin, isopropyl myristate, propylene glysol, triilsopropanolamine, water